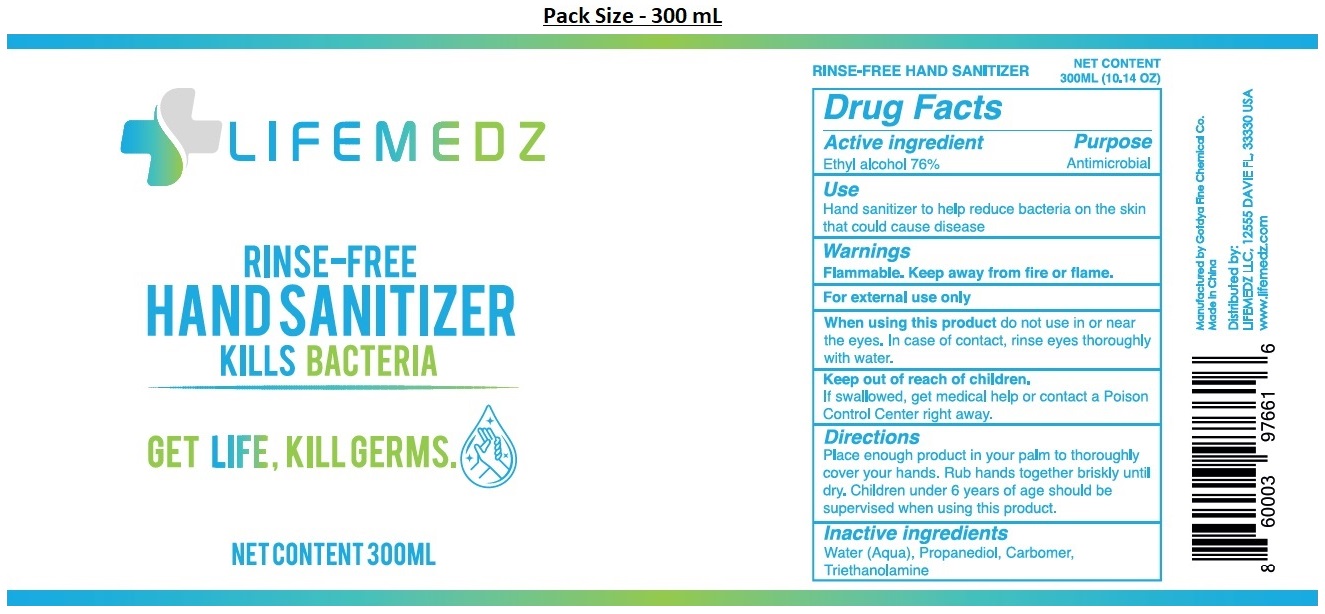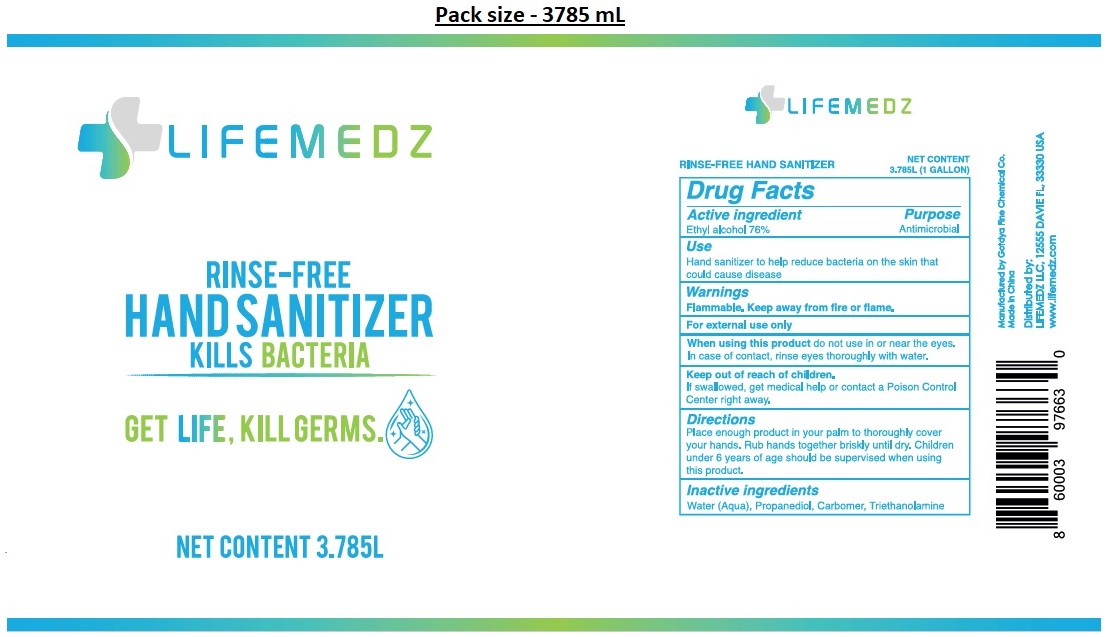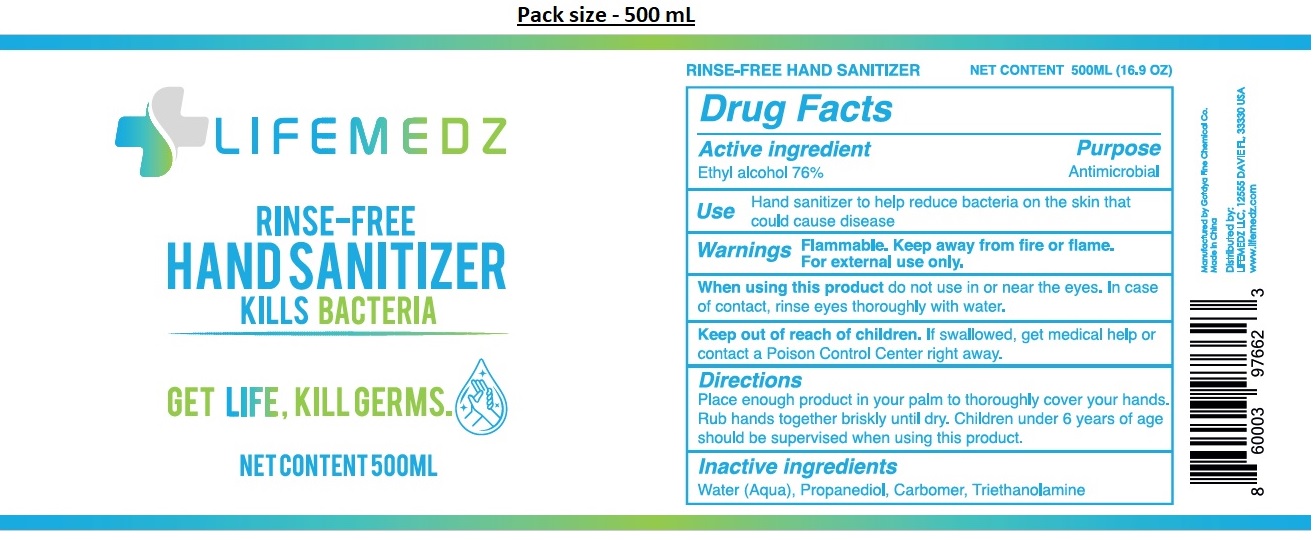 DRUG LABEL: LIFEMEDZ Rinse-FREE HAND SANITIZER
NDC: 78500-101 | Form: GEL
Manufacturer: Lifemedz Llc
Category: otc | Type: HUMAN OTC DRUG LABEL
Date: 20220511

ACTIVE INGREDIENTS: ALCOHOL 76 mL/100 mL
INACTIVE INGREDIENTS: WATER; PROPANEDIOL; CARBOMER HOMOPOLYMER, UNSPECIFIED TYPE; TROLAMINE

LIFEMEDZ RINSE-FREE HAND SANITIZER

Active ingredient

Ethyl alcohol 76%

Purpose

Antimicrobial

Use

Hand sanitizer to help reduce bacteria on the skin that could cause disease

Warnings

Flammable. Keep away from fire or flame.
For external use only
When using this product do not use in or near the eyes. In case of contact, rinse eyes thoroughly with water.

Keep out of reach of children.

If swallowed, get medical help or contact a Poison Control Center right away.

Directions

Place enough product in your palm to thoroughly cover your hands. Rub hands together briskly until dry. Children under 6 years of age should be supervised when using this product.

Inactive ingredients

Water (Aqua), Propanediol, Carbomer, Triethanolamine

KILLS BACTERIA
GET LIFE, KILL GERMS.

Manufactured by Gotdya Fine Chemical Co.

Made in China

Distributed by:

LIFEMEDZ LLC, 12555 DAVIE FL, 33330 USA

www.lifemedz.com